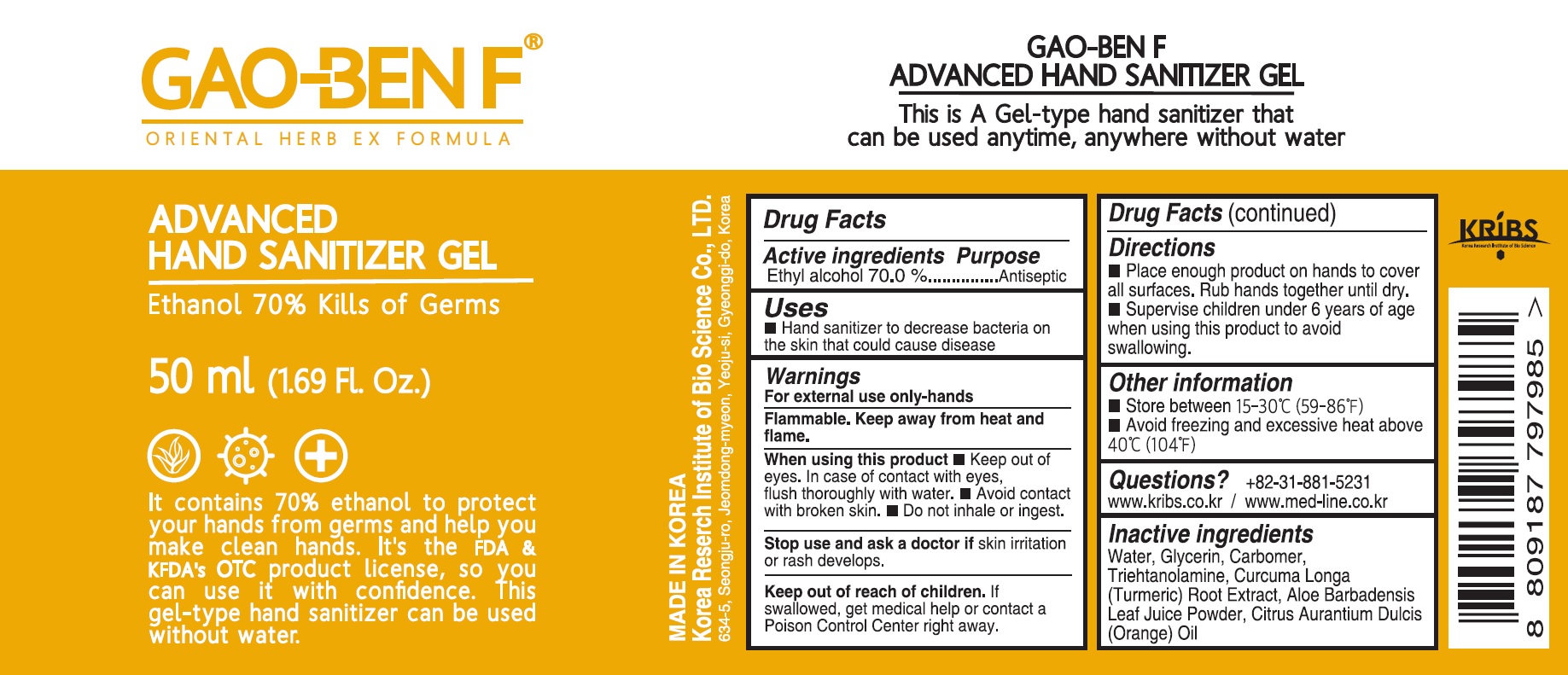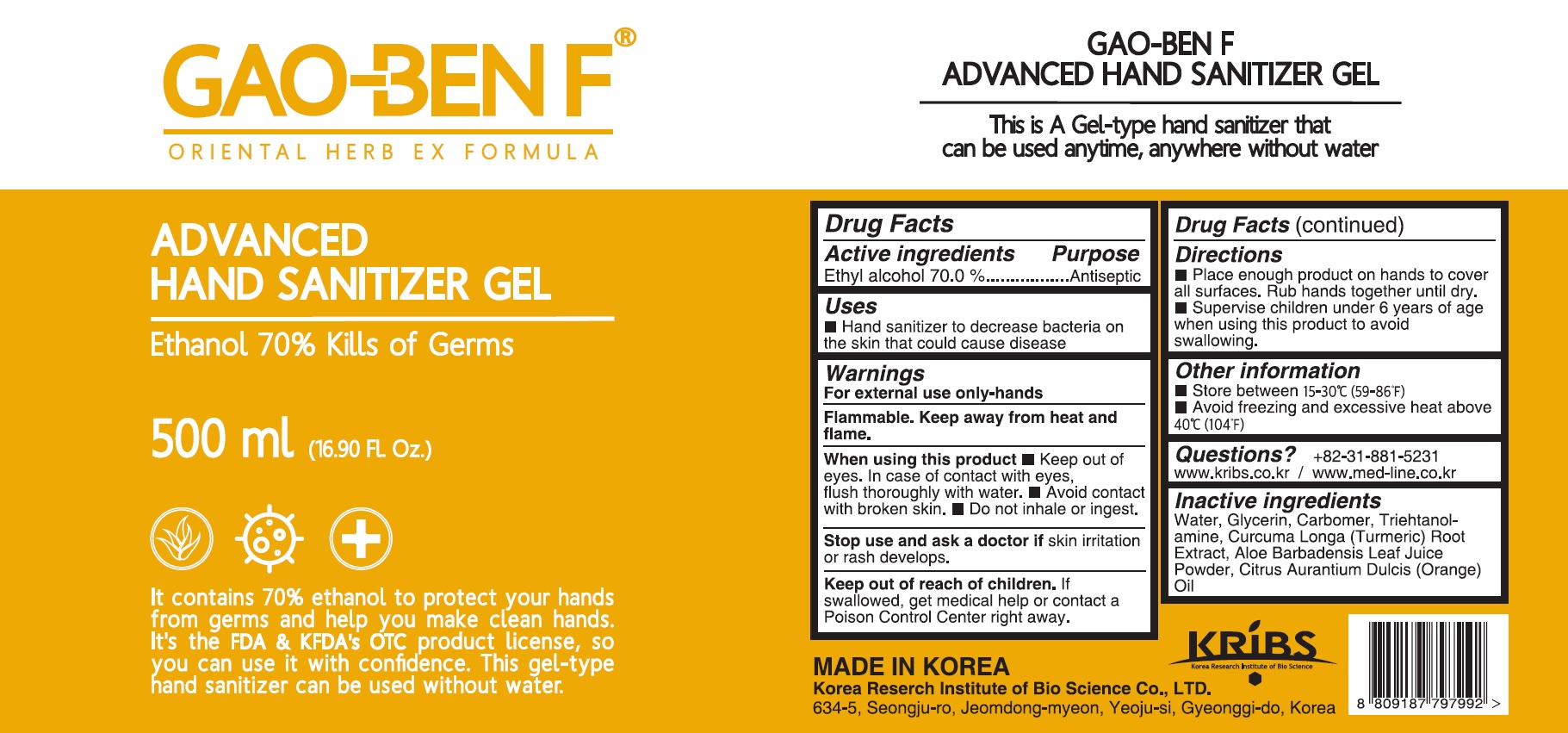 DRUG LABEL: GAO BEN F ADVANCED HAND SANITIZER
NDC: 76683-010 | Form: GEL
Manufacturer: KRIBS Co., Ltd.
Category: otc | Type: HUMAN OTC DRUG LABEL
Date: 20200427

ACTIVE INGREDIENTS: ALCOHOL 70 mL/100 mL
INACTIVE INGREDIENTS: Water; Glycerin; CARBOMER HOMOPOLYMER, UNSPECIFIED TYPE; TROLAMINE; TURMERIC; ALOE VERA LEAF; ORANGE OIL

ACTIVE INGREDIENT

Active ingredients: Ethyl alcohol 70%

INACTIVE INGREDIENT

Inactive ingredients:

Water, Glycerin, Carbomer, Triehtanolamine, Curcuma Longa (Turmeric) Root Extract, Aloe Barbadensis Leaf Juice Powder, Citrus Aurantium Dulcis (Orange) Oil

PURPOSE

Purpose: Antiseptic

WARNINGS

For external use only-hands

Flammable. Keep away from heat and flame.

When using this product ■ Keep out of eyes. In case of contact with eyes, flush thoroughly with water. ■ Avoid contact with broken skin. ■ Do not inhale or ingest.

Stop use and ask a doctor if skin irritation or rash develops.

Keep out of reach of children. If swallowed, get medical help or contact a Poison Control Center right away.

Uses

■ Hand sanitizer to decrease bacteria on the skin that could cause disease

Directions

■ Place enough product on hands to cover all surfaces. Rub hands together until dry.
■ Supervise children under 6 years of age when using this product to avoid swallowing.

Other information

■ Store between 15-30C (59-86F)
■ Avoid freezing and excessive heat above 40C (104F)

Questions

+82-31-881-5231 www.kribs.co.kr/www.med-line.co.kr